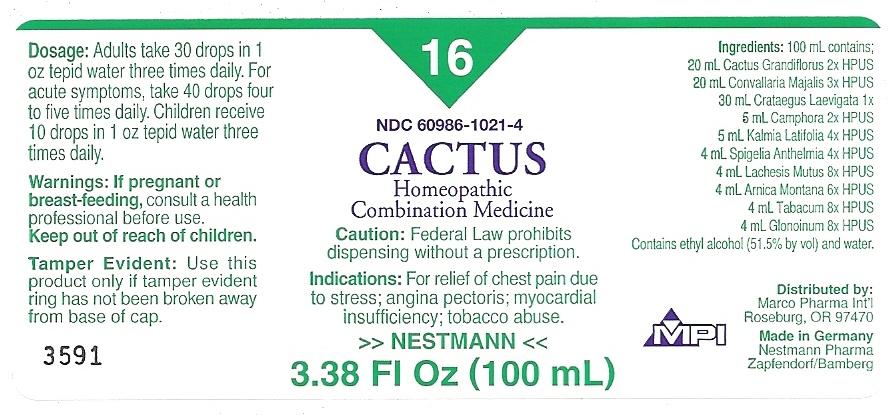 DRUG LABEL: CACTUS
NDC: 60986-1021 | Form: LIQUID
Manufacturer: Marco Pharma International LLC.
Category: homeopathic | Type: HUMAN PRESCRIPTION DRUG LABEL
Date: 20111205

ACTIVE INGREDIENTS: SELENICEREUS GRANDIFLORUS STEM 2 [hp_X]/100 mL; CONVALLARIA MAJALIS 3 [hp_X]/100 mL; CRATAEGUS LAEVIGATA WHOLE 1 [hp_X]/100 mL; CAMPHOR (NATURAL) 2 [hp_X]/100 mL; KALMIA LATIFOLIA LEAF 4 [hp_X]/100 mL; SPIGELIA ANTHELMIA 4 [hp_X]/100 mL; LACHESIS MUTA VENOM 8 [hp_X]/100 mL; ARNICA MONTANA 6 [hp_X]/100 mL; TOBACCO LEAF 8 [hp_X]/100 mL; NITROGLYCERIN 8 [hp_X]/100 mL
INACTIVE INGREDIENTS: ALCOHOL; WATER

Drug Facts

Active Ingredients

CACTUS GRANDIFLORUS 2XHPUS

CONVALLARIA MAJALIS 3XHPUS

CRATAEGUS LAEVIGATA 1XHPUS

CAMPHORA 2XHPUS

KALMIA LATIFOLIA 4XHPUS

SPIGELIA ANTHELMIA 4XHPUS

LACHESIS MUTUS 8XHPUS

ARNICA MONTANA 6XHPUS

TABACUM 8XHPUS

GLONOINUM 8XHPUS

The letters HPUS indicates that the components in this product are officially monographed in the Homeopathic Pharmacopoeia of United Sates.

Purpose

FOR RELIEF OF CHEST PAIN DUE TO STRESS; ANGINA PECTORIS; MYOCARDIAL INSUFFICIENCY; TOBACCO ABUSE.

Keep out of reach of children.

Suggested use

Error

Warnings

If pregnant or breast-feeding, consult a health professional before use.

DOSAGE AND ADMINISTRATION

(Read Suggested Use Section)

Inactive Ingredients

CONTAINS Ethyl Alcohol (51.5% by vol.) and Water

PACKAGE LABEL

MM1